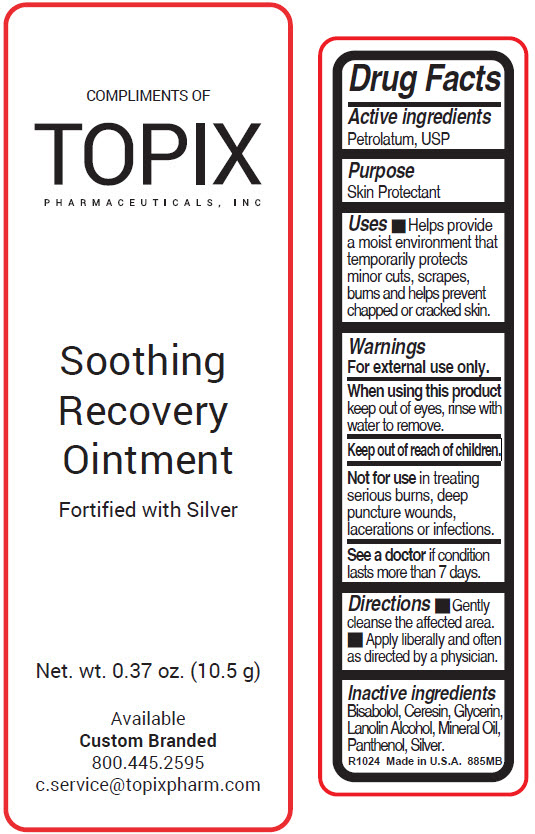 DRUG LABEL: Perfect 10 Soothing Recovery
NDC: 51326-885 | Form: OINTMENT
Manufacturer: Topiderm, Inc.
Category: otc | Type: HUMAN OTC DRUG LABEL
Date: 20250430

ACTIVE INGREDIENTS: PETROLATUM 84 mg/1 g
INACTIVE INGREDIENTS: .ALPHA.-BISABOLOL, (+/-)-; CERESIN; GLYCERIN; LANOLIN ALCOHOLS; MINERAL OIL; PANTHENOL; SILVER

Perfect 10 Soothing Recovery

Drug Facts

Active ingredients

Petrolatum, USP

Purpose

Skin Protectant

Uses

- Helps provide a moist environment that temporarily protects minor cuts, scrapes, burns and helps prevent chapped or cracked skin.

Warnings

For external use only.

When using this product keep out of eyes, rinse with water to remove.

Keep out of reach of children.

DO NOT USE

Not for use in treating serious burns, deep puncture wounds, lacerations or infections.

ASK DOCTOR

See a doctor if condition lasts more than 7 days.

Directions

- Gently cleanse the affected area.
- Apply liberally and often as directed by a physician.

Inactive ingredients

Bisabolol, Ceresin, Glycerin, Lanolin Alcohol, Mineral Oil, Panthenol, Silver.

PRINCIPAL DISPLAY PANEL - 10.5 g Tube Label

COMPLIMENTS OF

TOPIX
PHARMACEUTICALS, INC

Soothing
Recovery
Ointment

Fortified with Silver

Net. wt. 0.37 oz. (10.5 g)

Available
Custom Branded
800.445.2595
c.service@topixpharm.com